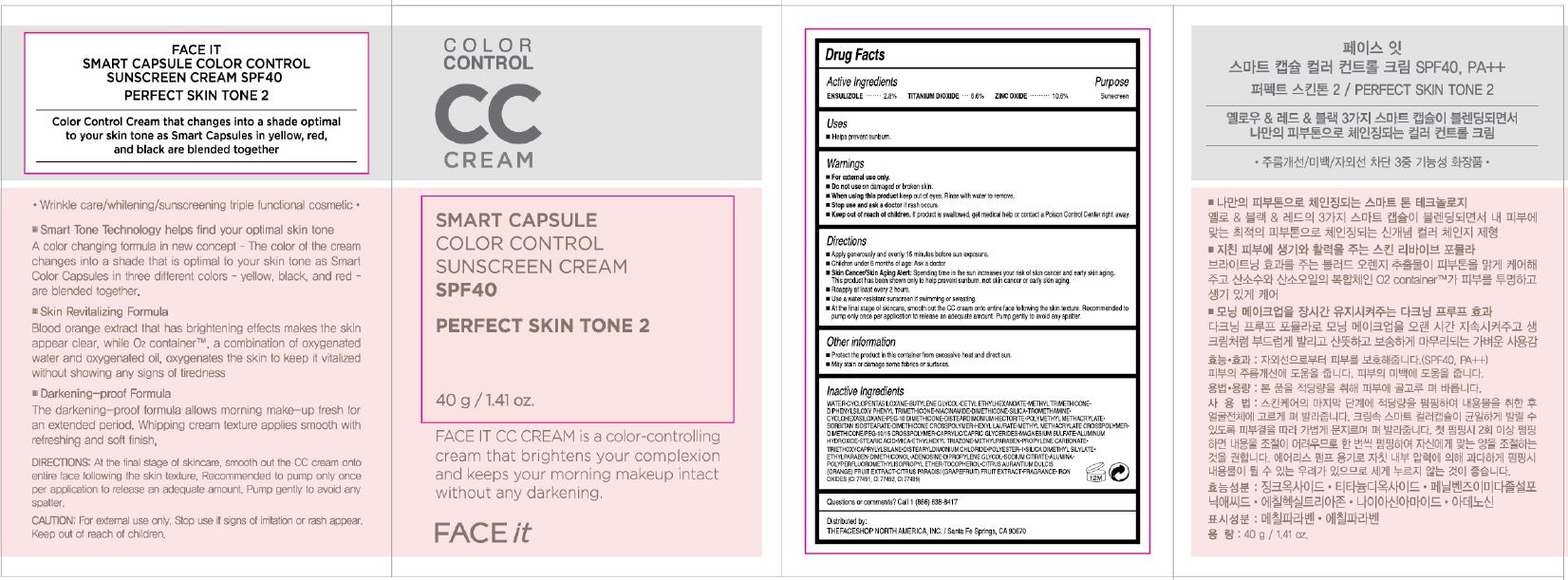 DRUG LABEL: FACE IT SMART COLOR CONTROL
NDC: 51523-677 | Form: CREAM
Manufacturer: THEFACESHOP CO., LTD.
Category: otc | Type: HUMAN OTC DRUG LABEL
Date: 20141120

ACTIVE INGREDIENTS: ENSULIZOLE 1.1 g/40 g; TITANIUM DIOXIDE 2.6 g/40 g; ZINC OXIDE 4.2 g/40 g
INACTIVE INGREDIENTS: WATER

Active Ingredients

ENSULIZOLE.............. 2.8%
TITANIUM DIOXIDE.. 6.6%
ZINC OXIDE.............. 10.6%

Purpose

Sunscreen

Sunscreen

Sunscreen

Warnings

For external use only.

Do not use on damaged or broken skin

When using this product keep out of eyes. Rinse with water to remove.

Stop use and ask a doctor if rash occurs.

Keep out of reach of children.

If product is swallowed, get medical help or contact a Poison Control Center right away

Directions

Apply generously and evenly 15 minutes before sun exposure.
Children under 6 months of age: Ask a doctor
Skin Cancer/Skin Aging Alert: Spending time in the sun increases your risk of skin cancer and early skin. aging. This product has been shown only to help prevent sunburn, not skin cancer or early skin aging.
Reapply at least every 2 hoursUse a water-resistant sunscreen if swimming or sweating.

At the final stage of skincare, smooth out the CC cream onto entire face following the skin texture.

Recommended to pump only once per application to release an adequate amount.

Pump gently to avoid any spatter.

Other Information

Protect the product in this container from excessive heat and direct sun

May stain or damage some fabrics or surfaces

Inactive Ingredients

WATER•CYCLOPENTASILOXANE•BUTYLENE GLYCOL•CETYL ETHYLHEXANOATE•METHYL TRIMETHICONE•
DIPHENYLSILOXY PHENYL TRIMETHICONE•NIACINAMIDE•DIMETHICONE•SILICA•TROMETHAMINE•
CYCLOHEXASILOXANE•PEG-10 DIMETHICONE•DISTEARDIMONIUM HECTORITE•POLYMETHYL METHACRYLATE•
SORBITAN ISOSTEARATE•DIMETHICONE CROSSPOLYMER•HEXYL LAURATE•METHYL METHACRYLATE CROSSPOLYMER•
DIMETHICONE/PEG-10/15 CROSSPOLYMER•CAPRYLIC/CAPRIC GLYCERIDES•MAGNESIUM SULFATE•ALUMINUM
HYDROXIDE•STEARIC ACID•MICA•ETHYLHEXYL TRIAZONE•METHYLPARABEN•PROPYLENE CARBONATE•
TRIETHOXYCAPRYLYLSILANE•DISTEARYLDIMONIUM CHLORIDE•POLYESTER-1•SILICA DIMETHYL SILYLATE•
ETHYLPARABEN•DIMETHICONOL•ADENOSINE•DIPROPYLENE GLYCOL•SODIUM CITRATE•ALUMINA•
POLYPERFLUOROMETHYLISOPROPYL ETHER•TOCOPHEROL•CITRUS AURANTIUM DULCIS
(ORANGE) FRUIT EXTRACT•CITRUS PARADISI (GRAPEFRUIT) FRUIT EXTRACT•FRAGRANCE•IRON
OXIDES (CI 77491, CI 77492, CI 77499)

Questions or comments? Call 1 (866) 638-8417

Distributed by:

THEFACESHOP NORTH AMERICA, INC. / Santa Fe Springs, CA 90670

PACKAGE LABEL

COLOR CONTROL CC CREAM
AURA COLOR CONTROL
SUNSCREEN CREAM (REFILL)
SPF30
02 NATURAL BEIGE

FACE IT CC CREAM is a color-controlling cream that brightens your complexion
and keeps your morning makeup intact without any darkening.

FACE it